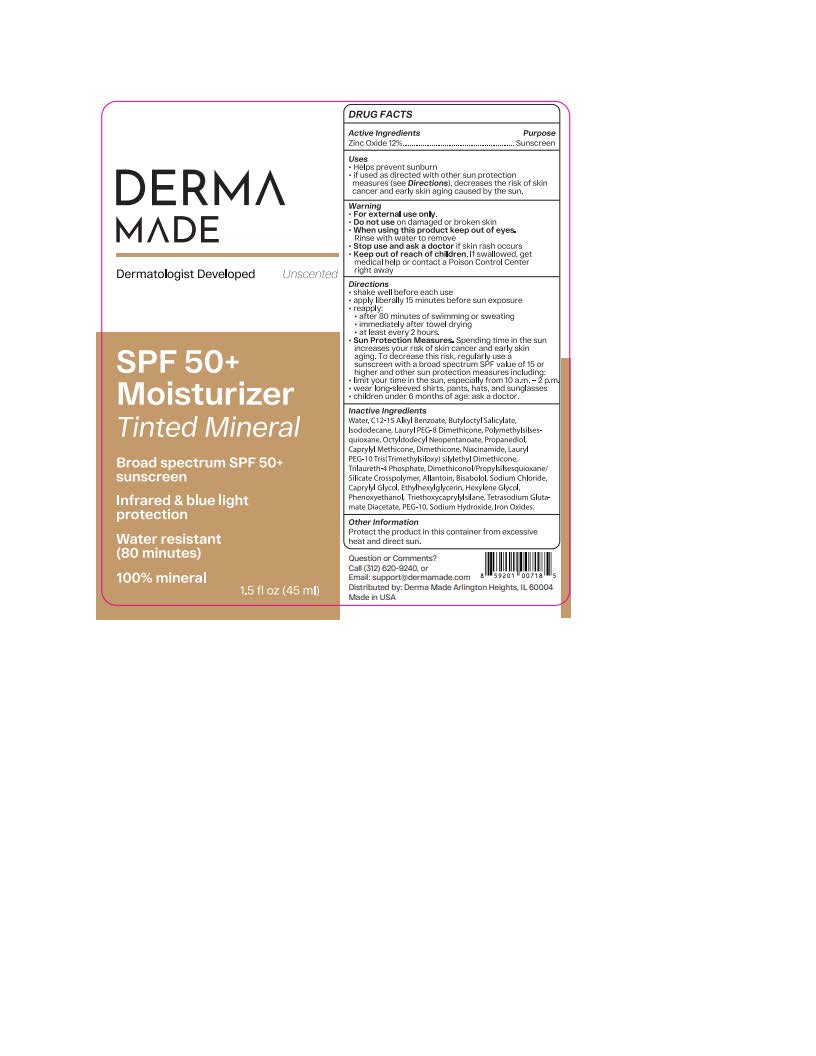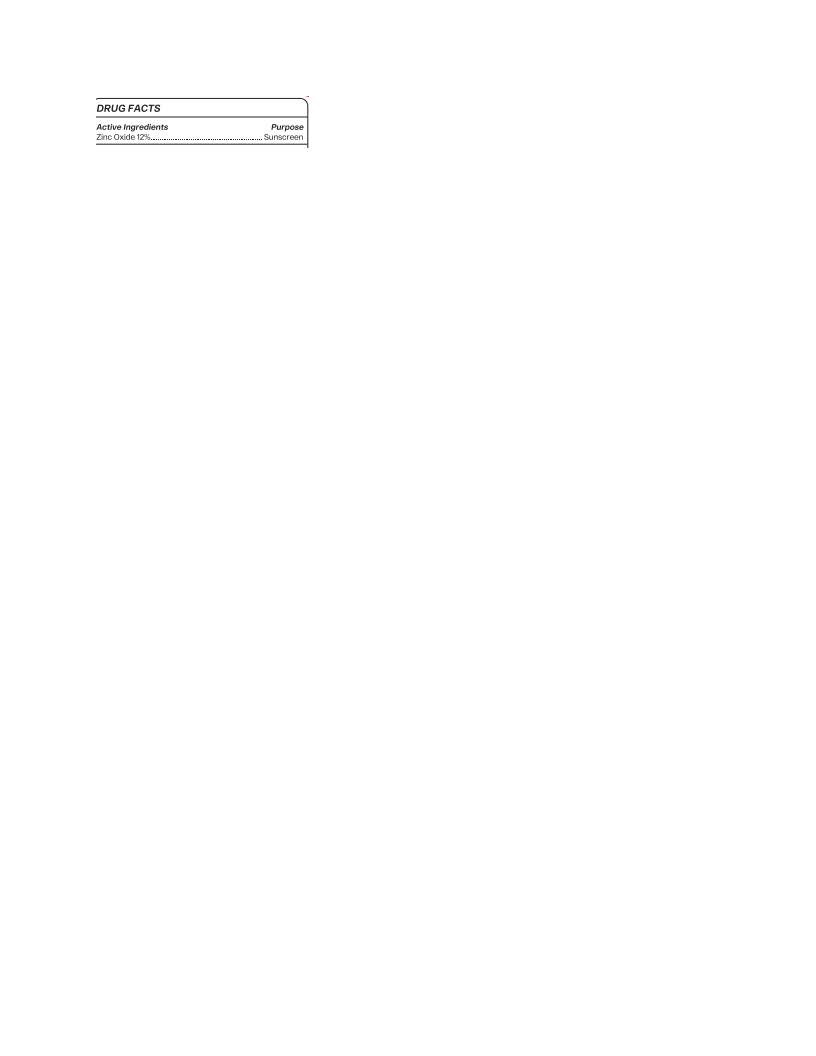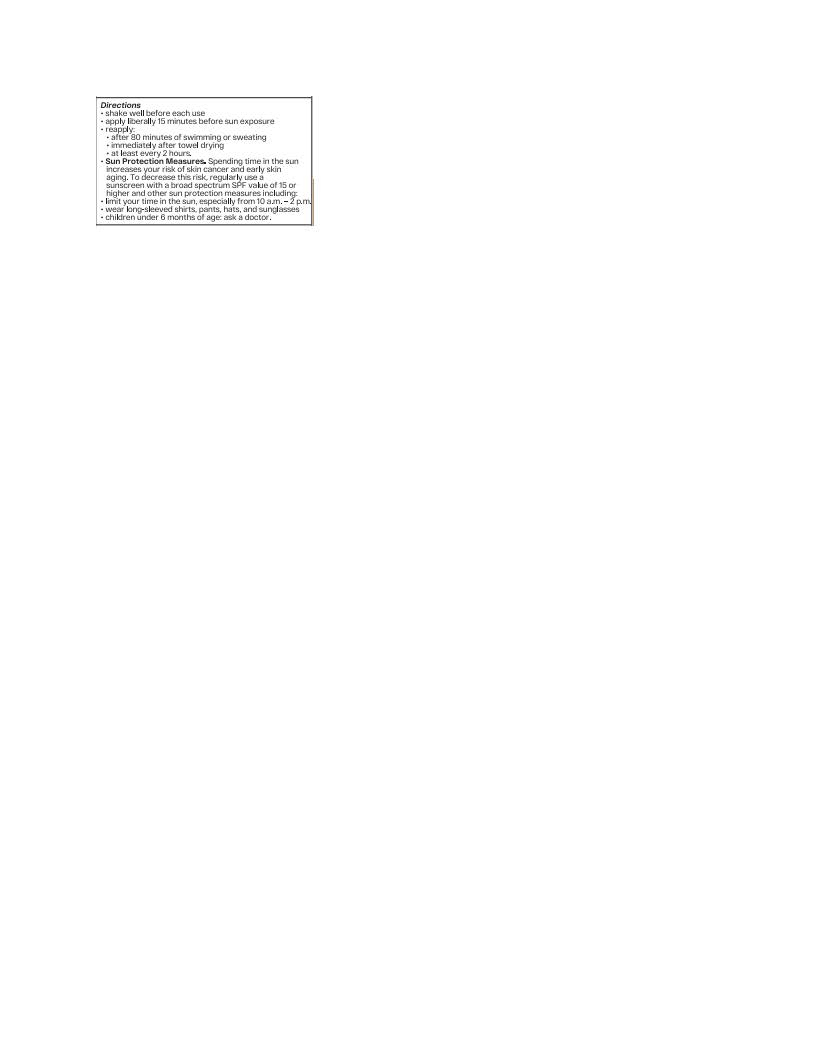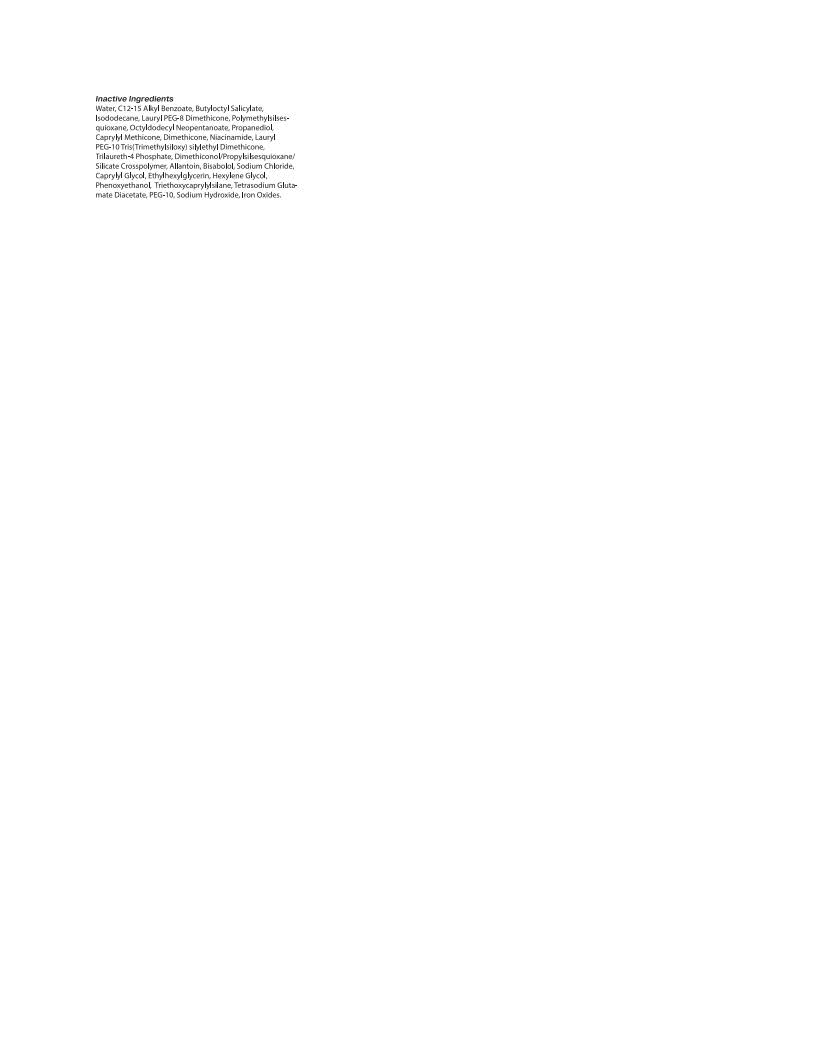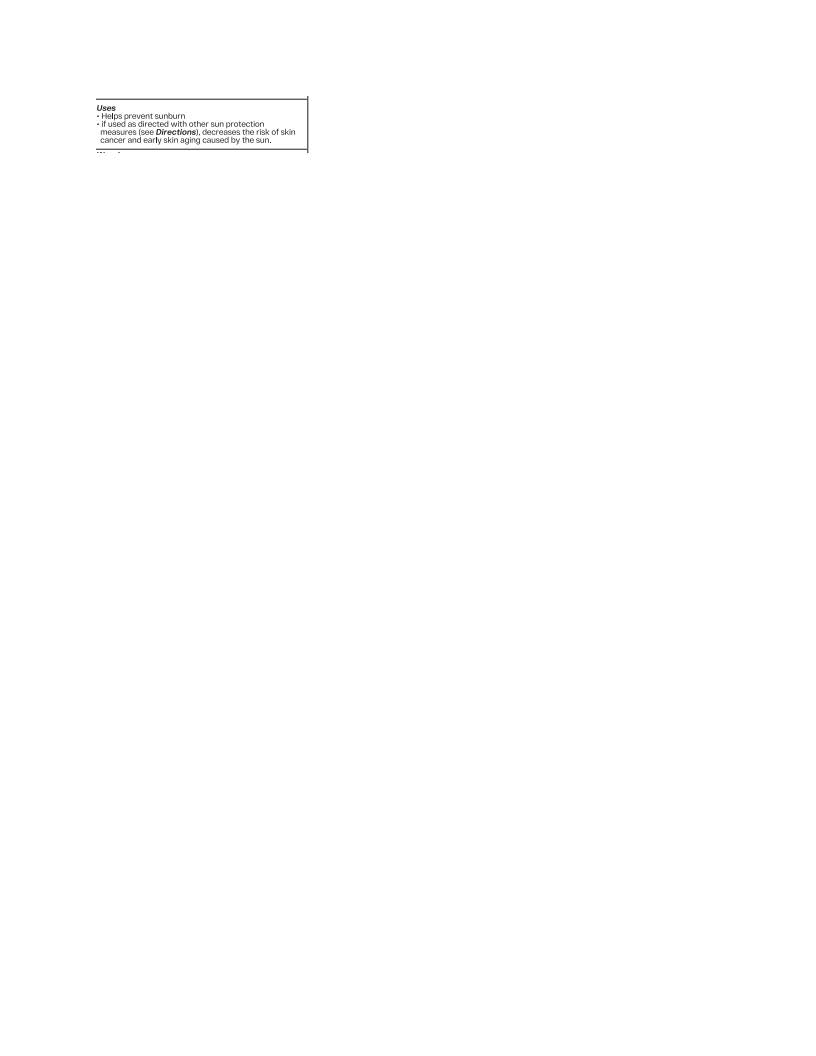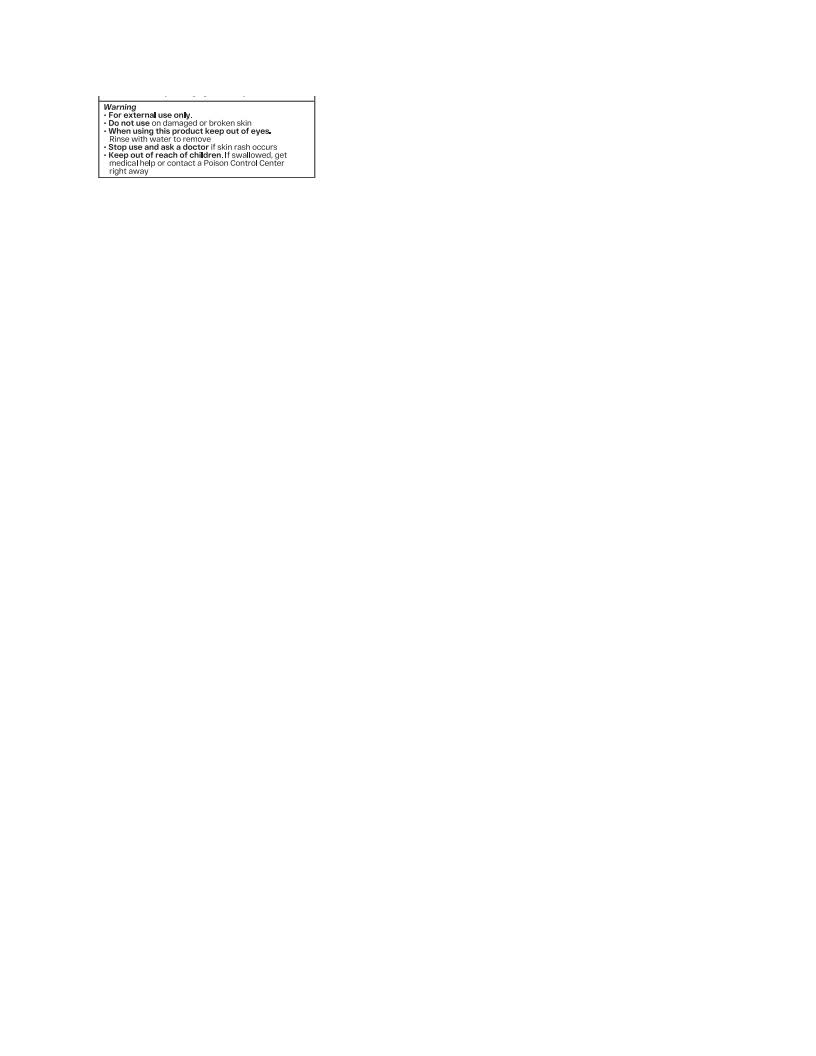 DRUG LABEL: Organys Derma Made
NDC: 83612-0330 | Form: LOTION
Manufacturer: Organys Beauty
Category: otc | Type: HUMAN OTC DRUG LABEL
Date: 20251009

ACTIVE INGREDIENTS: ZINC OXIDE 132 mg/1 mL
INACTIVE INGREDIENTS: NIACINAMIDE; ETHYLHEXYLGLYCERIN; HEXYLENE GLYCOL; GLYCERIN; DIMETHICONOL/PROPYLSILSESQUIOXANE/SILICATE CROSSPOLYMER (450000000 MW); PROPANEDIOL; TETRASODIUM GLUTAMATE DIACETATE; CARRAGEENAN; SODIUM CHLORIDE; PHENOXYETHANOL; PALMITOYL TRIPEPTIDE-1; .BETA.-TOCOPHEROL; POLYMETHYLSILSESQUIOXANE (4.5 MICRONS); PALMITOYL TETRAPEPTIDE-7; TRILAURETH-4 PHOSPHATE; BUTYLOCTYL SALICYLATE; OCTYLDODECYL NEOPENTANOATE; ISODODECANE; .ALPHA.-BISABOLOL, (+)-; BUTYLENE GLYCOL; POLYSORBATE 20; SODIUM HYDROXIDE; WATER

Organys Derma Made